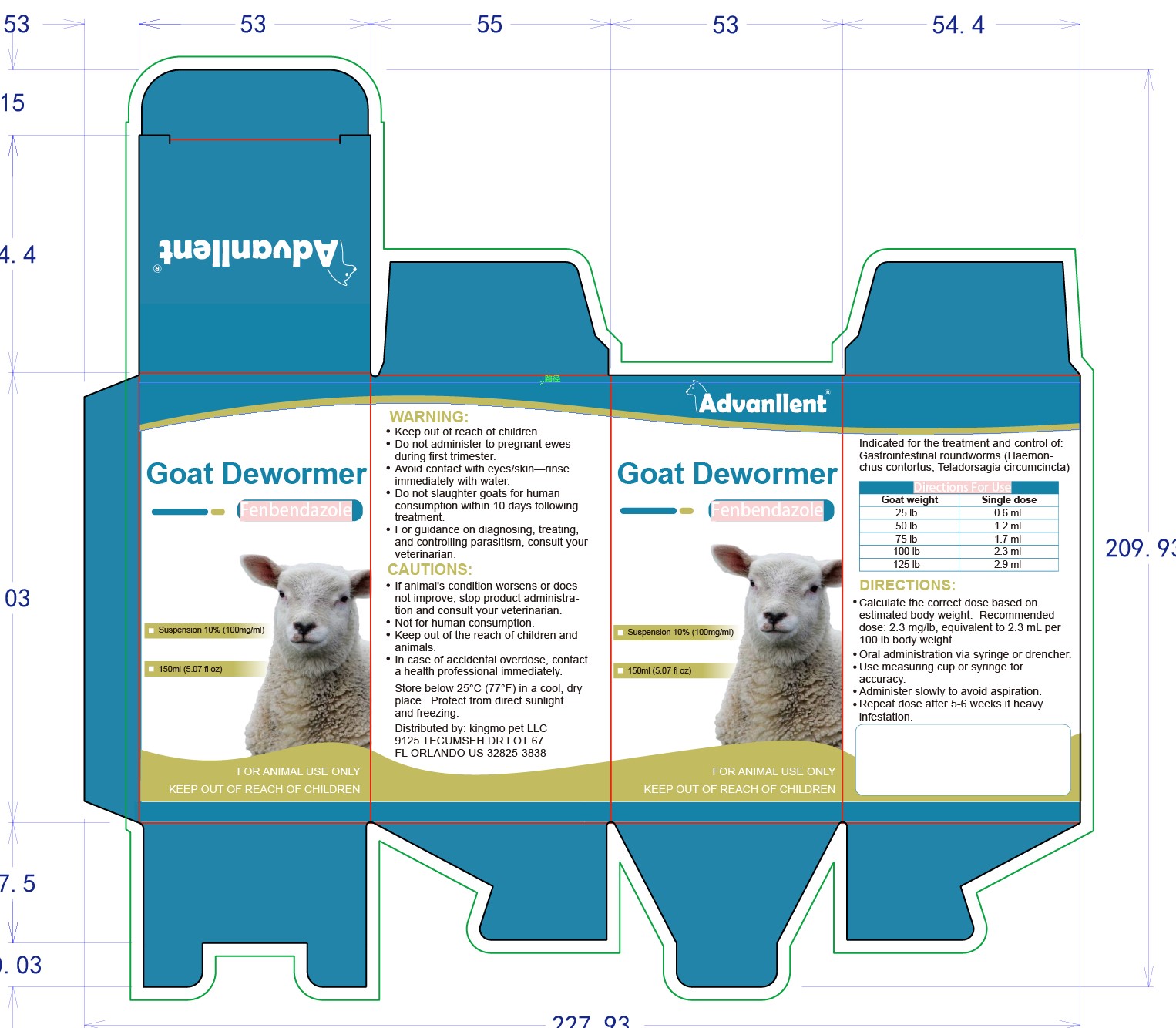 DRUG LABEL: goat dewormer
NDC: 86216-007 | Form: SUSPENSION
Manufacturer: Pet Professional inc.
Category: animal | Type: OTC ANIMAL DRUG LABEL
Date: 20251201

ACTIVE INGREDIENTS: FENBENDAZOLE 100 mg/1 mL
INACTIVE INGREDIENTS: WATER 900 mg/1 mL

goat dewormer

Direction

Calculate the correct dose based on estimated body weight. Recommended dose: 2.3 mg/lb, equivalent to 2.3 mL per 100 lb body weight.

Oral administration via syringe or drencher.

Use measuring cup or syringe for accuracy.

Administer slowly to avoid aspiration.

Repeat dose after 5-6 weeks if heavyinfestation.